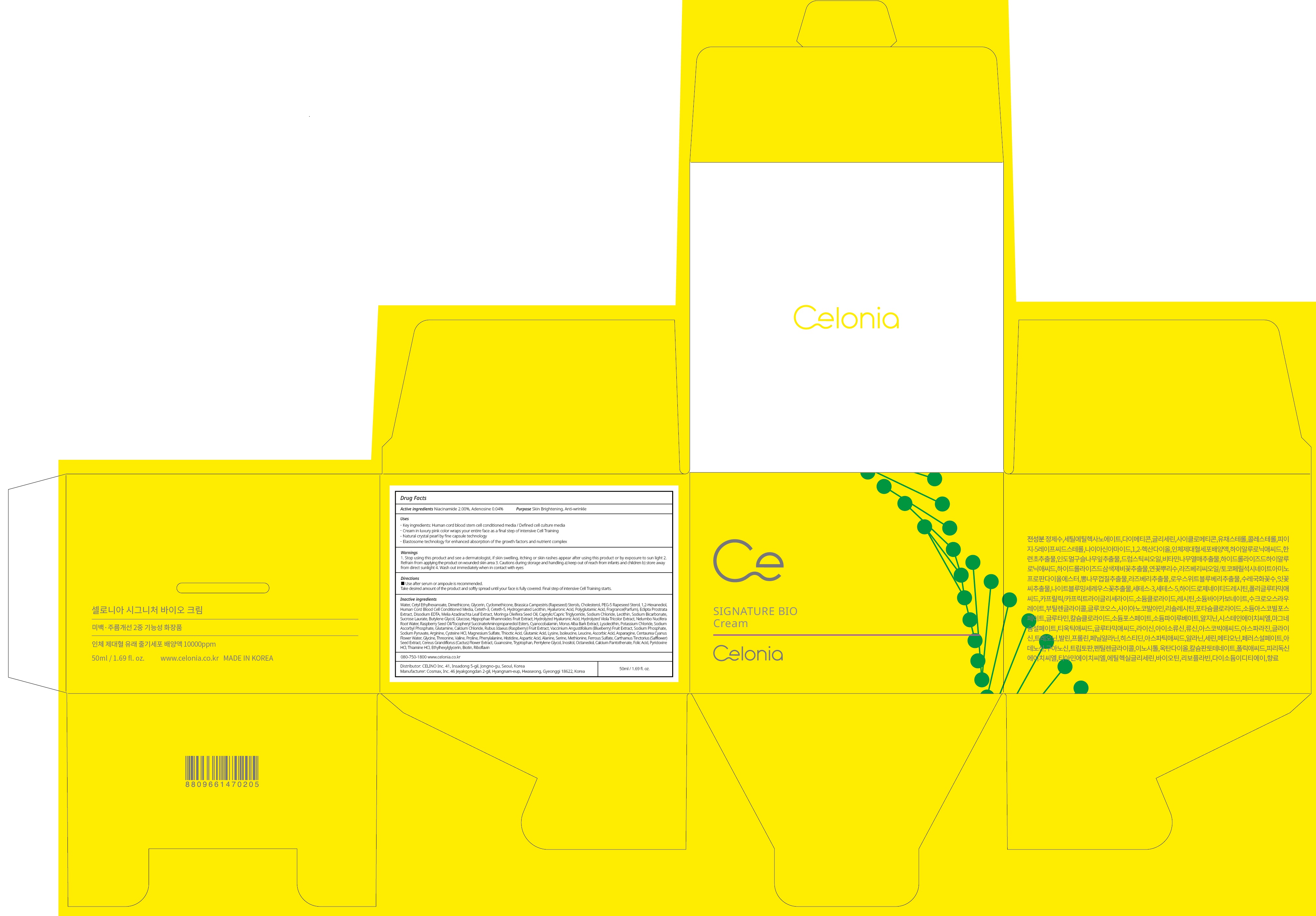 DRUG LABEL: CELONIA SIGNATURE BIO
NDC: 73655-020 | Form: CREAM
Manufacturer: Celino Inc.
Category: otc | Type: HUMAN OTC DRUG LABEL
Date: 20200310

ACTIVE INGREDIENTS: Niacinamide 1.00 g/50 mL; Adenosine 0.02 g/50 mL
INACTIVE INGREDIENTS: Water; Cetyl Ethylhexanoate

ACTIVE INGREDIENT

Active ingredients: Niacinamide 2.00%, Adenosine 0.04%

INACTIVE INGREDIENT

Inactive ingredients:

Water, Cetyl Ethylhexanoate, Dimethicone, Glycerin, Cyclomethicone, Brassica Campestris (Rapeseed) Sterols, Cholesterol, PEG-5 Rapeseed Sterol, 1,2-Hexanediol, Human Cord Blood Cell Conditioned Media, Ceteth-3, Ceteth-5, Hydrogenated Lecithin, Hyaluronic Acid, Polyglutamic Acid, Fragrance(Parfum), Eclipta Prostrata Extract, Disodium EDTA, Melia Azadirachta Leaf Extract, Moringa Oleifera Seed Oil, Caprylic/Capric Triglyceride, Sodium Chloride, Lecithin, Sodium Bicarbonate, Sucrose Laurate,
Butylene Glycol, Glucose, Hippophae Rhamnoides Fruit Extract, Hydrolyzed Hyaluronic Acid, Hydrolyzed Viola Tricolor Extract, Nelumbo Nucifera Root Water, Raspberry Seed Oil/Tocopheryl SuccinateAminopropanediol Esters, Cyanocobalamin, Morus Alba Bark Extract, Lysolecithin, Potassium Chloride, Sodium Ascorbyl Phosphate, Glutamine, Calcium Chloride, Rubus Idaeus (Raspberry) Fruit Extract, Vaccinium Angustifolium (Blueberry) Fruit Extract, Sodium Phosphate, Sodium Pyruvate, Arginine, Cysteine HCl, Magnesium Sulfate, Thioctic Acid, Glutamic Acid, Lysine, Isoleucine, Leucine, Ascorbic Acid, Asparagine, Centaurea Cyanus Flower Water, Glycine, Threonine, Valine, Proline, Phenylalanine, Histidine, Aspartic Acid, Alanine, Serine, Methionine, Ferrous Sulfate, Carthamus Tinctorius (Safflower) Seed Extract, Cereus Grandiflorus (Cactus) Flower Extract, Guanosine, Tryptophan, Pentylene Glycol, Inositol, Octanediol, Calcium Pantothenate, Folic Acid, Pyridoxine HCl, Thiamine HCl, Ethylhexylglycerin, Biotin, Riboflavin

PURPOSE

Purpose: Skin Brightening, Anti-wrinkle

WARNINGS

1. Stop using this product and see a dermatologist, if skin swelling, itching or skin rashes appear after using this product or by exposure to sun light

2. Refrain from applying the product on wounded skin area

3. Cautions during storage and handling a) keep out of reach from infants and children b) store away from direct sunlight

4. Wash out immediately when in contact with eyes

KEEP OUT OF REACH OF CHILDREN

keep out of reach from infants and children

QUESTIONS

080-750-1800

www.celonia.co.kr

Uses

Key ingredients: Human cord blood stem cell conditioned media / Defined cell culture media
Cream in luxury pink color wraps your entire face as a final step of intensive Cell Training
Natural crystal pearl by fine capsule technology
Elastosome technology for enhanced absorption of the growth factors and nutrient complex

Directions

Use after serum or ampoule is recommended. Take desired amount of the product and softly spread until your face is fully covered. Final step of intensive Cell Training starts.